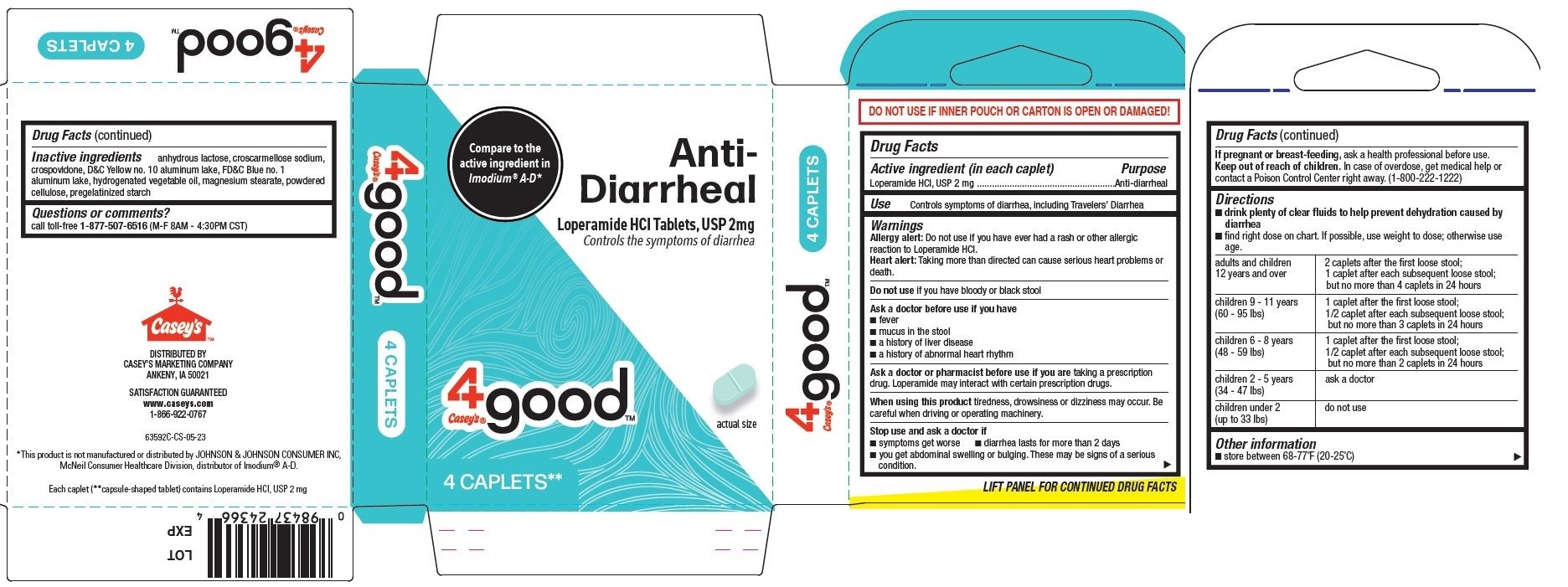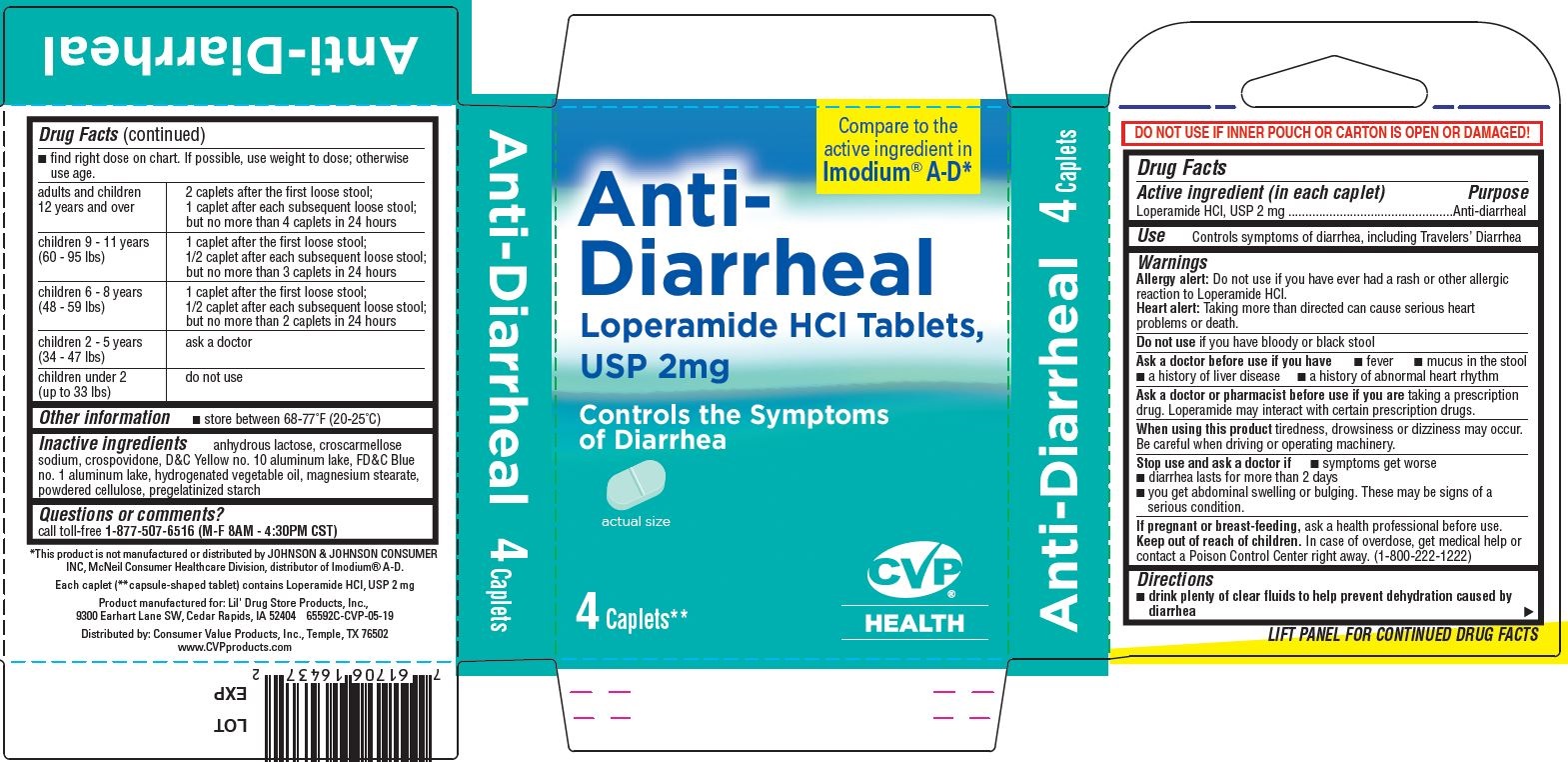 DRUG LABEL: Anti-Diarrheal, Caseys 4good
NDC: 66715-6359 | Form: TABLET
Manufacturer: Lil' Drug Store Products, Inc.
Category: otc | Type: HUMAN OTC DRUG LABEL
Date: 20241229

ACTIVE INGREDIENTS: LOPERAMIDE HYDROCHLORIDE 2 mg/1 1
INACTIVE INGREDIENTS: CROSPOVIDONE (15 MPA.S AT 5%); D&C YELLOW NO. 10; STARCH, CORN; POWDERED CELLULOSE; ANHYDROUS LACTOSE; FD&C BLUE NO. 1; HYDROGENATED COTTONSEED OIL; CROSCARMELLOSE SODIUM; MAGNESIUM STEARATE

Anti-Diarrheal

Drug Facts

Active ingredient

Active ingredient (in each caplet)

Loperamide HCl, USP 2 mg

Purpose

Anti-diarrheal

Use

Controls symptoms of diarrhea, including Travelers’ Diarrhea

Warnings

Allergy alert

Allergy alert:Do not use if you have ever had a rash or other allergic reaction to Loperamide HCl.

Heart alert

Heart alert:Taking more than directed can cause serious heart problems or death.

Do not use

Do not useif you have bloody or black stool

Ask a doctor before use if you have

- fever
- mucus in the stool
- a history of liver disease
- a history of abnormal heart rhythm

Ask a doctor or pharmacist before use if you aretaking a prescription drug. Loperamide may interact with certain prescription drugs.

When using this product

When using this producttiredness, drowsiness or dizziness may occur. Be careful when driving or operating machinery.

Stop use and ask a doctor if

- symptoms get worse
- diarrhea lasts for more than 2 days
- you get abdominal swelling or bulging. These may be signs of a serious condition.

If pregnant or breast-feeding,ask a health professional before use.

Keep out of reach of children.In case of overdose, get medical help or contact a Poison Control Center right away. (1-800-222-1222)

Directions

- drink plenty of clear fluids to help prevent dehydration caused by diarrhea
- find right dose on chart. If possible, use weight to dose; otherwise use age.

adults and children 12 years and over | 2 caplets after the first loose stool; 1 caplet after each subsequent loose stool; but no more than 4 caplets in 24 hours
children 9 - 11 years (60 - 95 lbs) | 1 caplet after the first loose stool; 1/2 caplet after each subsequent loose stool; but no more than 3 caplets in 24 hours
children 6 - 8 years (48 - 59 lbs) | 1 caplet after the first loose stool; 1/2 caplet after each subsequent loose stool; but no more than 2 caplets in 24 hours
children 2 - 5 years (34 - 47 lbs) | ask a doctor
children under 2 (up to 33 lbs) | do not use

Other information

- store between 68-77°F (20-25°C)

Inactive ingredients

anhydrous lactose, croscarmellose sodium, crospovidone, D&C Yellow no. 10 aluminum lake, FD&C Blue no. 1 aluminum lake, hydrogenated vegetable oil, magnesium stearate, powdered cellulose, pregelatinized starch

Questions or comments?

call toll-free 1-877-507-6516(M-F 8AM - 4:30PM CST)

Anti-Diarrheal 4ct, CVP®HEALTH

Compare to the
active ingredient in
Imodium®A-D*

Anti-
Diarrheal

Loperamide HCl Tablets,
USP 2mg

Controls the Symptoms
of Diarrhea

[caplet image]

actual size

4 Caplets*

CVP®

HEALTH

Anti-Diarrheal 4ct, Casey's 4goodTM

Compare to the
active ingredient in
Imodium®A-D*

Anti-
Diarrheal
Loperamide HCI Tablets, USP 2mg
Controls the symptoms of diarrhea

[Casey's logo]

[caplet image]

actual size

4 CAPLETS**